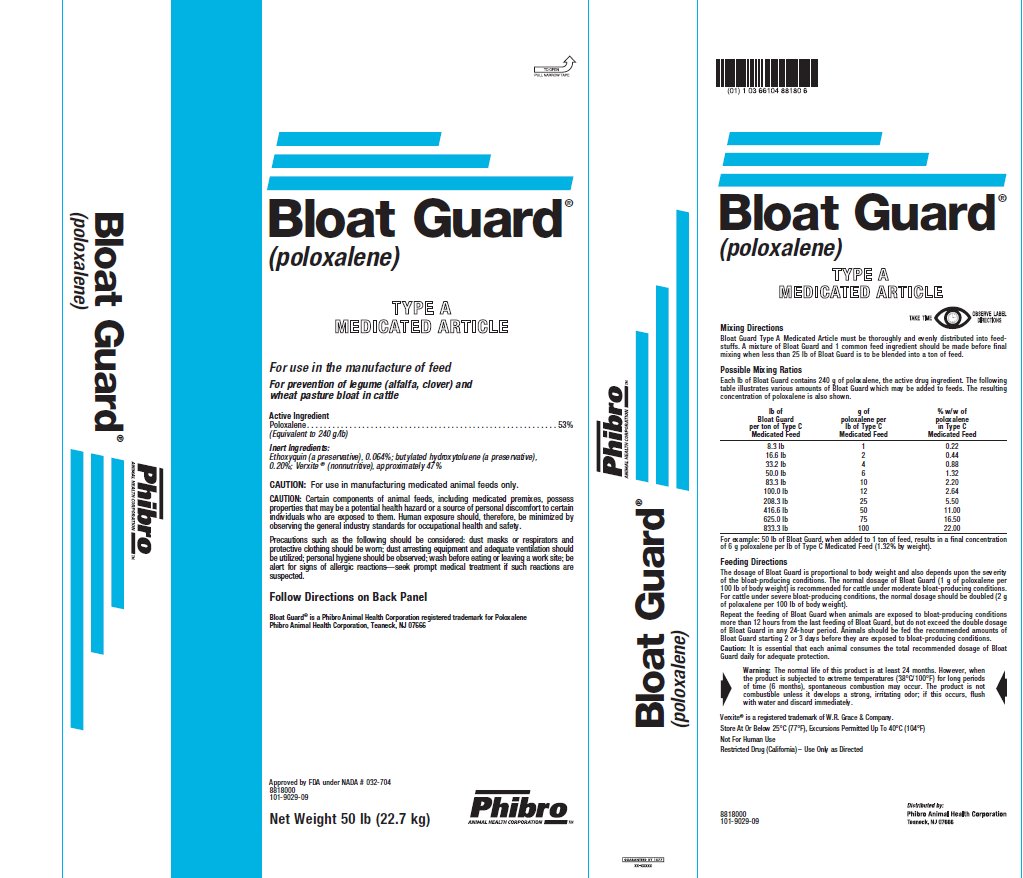 DRUG LABEL: Bloat Guard
NDC: 66104-2301 | Form: POWDER
Manufacturer: Phibro Animal Health
Category: animal | Type: OTC TYPE A MEDICATED ARTICLE ANIMAL DRUG LABEL
Date: 20190627

ACTIVE INGREDIENTS: POLOXALENE 240 g/0.45 kg
INACTIVE INGREDIENTS: BUTYLATED HYDROXYTOLUENE; ETHOXYQUIN

Bloat Guard®
(poloxalene)
TYPE A MEDICATED ARTICLE

INDICATIONS AND USAGE

For use in the manufacture of feed

For prevention of legume (alfalfa, clover) and wheat pasture bloat in cattle

Active Ingredient

Poloxalene . . . . . . . . . . . . . . . . . . . . . . . . . . . . . . . . . . . . . . . . . . . . . . . . . . . . . . . 53%

(Equivalent to 240 g/lb)

Inert Ingredients:

Ethoxyquin (a preservative), 0.064%; butylated hydroxytoluene (a preservative), 0.20%; Verxite ® (nonnutritive), approximately 47%

CAUTION:

For use in manufacturing medicated animal feeds only.

CAUTION: Certain components of animal feeds, including medicated premixes, possess properties that may be a potential health hazard or a source of personal discomfort to certain individuals who are exposed to them. Human exposure should, therefore, be minimized by observing the general industry standards for occupational health and safety.

Precautions such as the following should be considered: dust masks or respirators and protective clothing should be worn; dust arresting equipment and adequate ventilation should be utilized; personal hygiene should be observed; wash before eating or leaving a work site; be alert for signs of allergic reactions—seek prompt medical treatment if such reactions are suspected.

Mixing Directions

Bloat Guard Type A Medicated Article must be thoroughly and evenly distributed into feedstuffs. A mixture of Bloat Guard and 1 common feed ingredient should be made before final mixing when less than 25 lb of Bloat Guard is to be blended into a ton of feed.

Possible Mixing Ratios

Each lb of Bloat Guard contains 240 g of poloxalene, the active drug ingredient. The following table illustrates various amounts of Bloat Guard which may be added to feeds. The resulting concentration of poloxalene is also shown.

lb of Bloat Guard per ton of Type C Medicated Feed | g of poloxalene per lb of Type C Medicated Feed | % w/w of poloxalene in Type C Medicated Feed
8.3 lb; 16.6 lb; 33.2 lb; 50.0 lb; 83.3 lb; 100.0 lb; 208.3 lb; 416.6 lb; 625.0 lb; 833.3 lb | 1; 2; 4; 6; 10; 12; 25; 50; 75; 100 | 0.22; 0.44; 0.88; 1.32; 2.20; 2.64; 5.50; 11.00; 16.50; 22.00

For example: 50 lb of Bloat Guard, when added to 1 ton of feed, results in a final concentration of 6 g poloxalene per lb of Type C Medicated Feed (1.32% by weight).

Feeding Directions

The dosage of Bloat Guard is proportional to body weight and also depends upon the severity of the bloat-producing conditions. The normal dosage of Bloat Guard (1 g of poloxalene per 100 lb of body weight) is recommended for cattle under moderate bloat-producing conditions. For cattle under severe bloat-producing conditions, the normal dosage should be doubled (2 g of poloxalene per 100 lb of body weight).

Repeat the feeding of Bloat Guard when animals are exposed to bloat-producing conditions more than 12 hours from the last feeding of Bloat Guard, but do not exceed the double dosage of Bloat Guard in any 24-hour period. Animals should be fed the recommended amounts of Bloat Guard starting 2 or 3 days before they are exposed to bloat-producing conditions.

Caution: It is essential that each animal consumes the total recommended dosage of Bloat Guard daily for adequate protection.

Warning:

The normal life of this product is at least 24 months. However, when the product is subjected to extreme temperatures (38°C/100°F) for long periods of time (6 months), spontaneous combustion may occur. The product is not combustible unless it develops a strong, irritating odor; if this occurs, flush with water and discard immediately.

.

NOT FOR HUMAN USE

RESTRICTED DRUG (CALIFORNIA) – USE ONLY AS DIRECTED

Follow Directions on Back Panel

Bloat Guard® is a Phibro Animal Health registered trademark for Poloxalene

Phibro Animal Health, Inc., Ridgefield Park, NJ 07660.

Net Weight 50 lb (22.7 kg)

Approved by FDA under NADA #032-704

8818000

101-9029-09

Verxite® is a registered trademark of W.R. Grace & Company